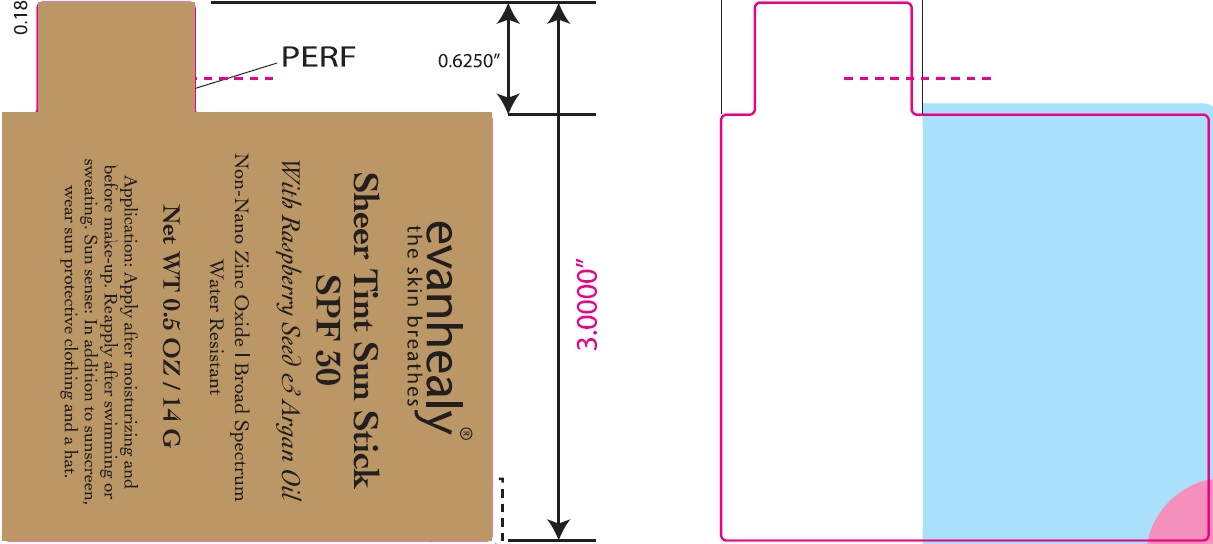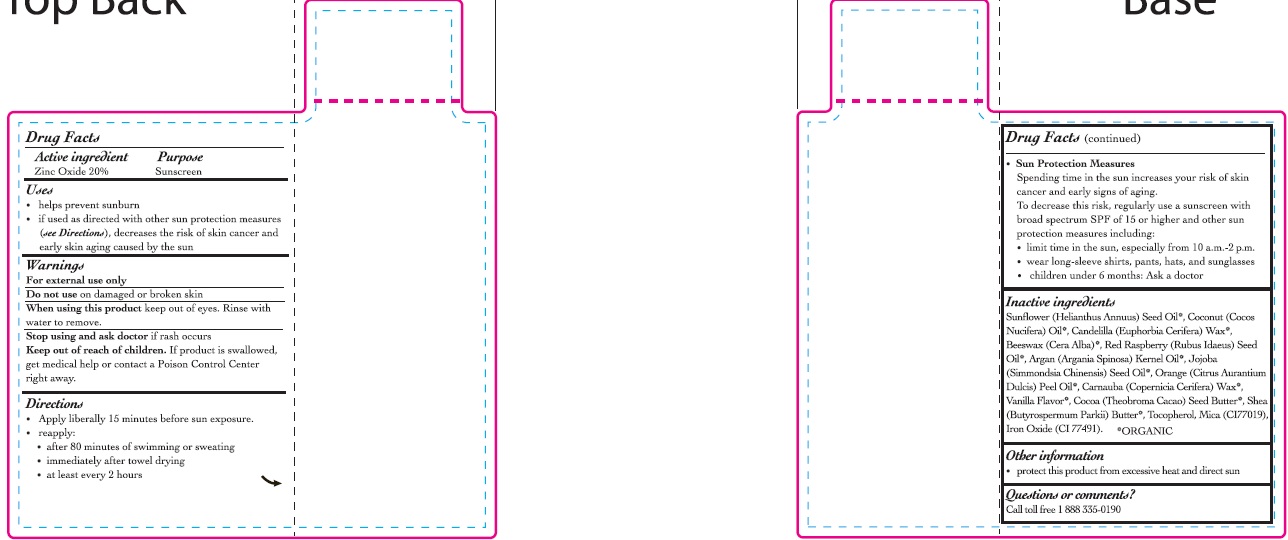 DRUG LABEL: SUNSCREEN
NDC: 62932-178 | Form: OINTMENT
Manufacturer: Private Label Select Ltd CO
Category: otc | Type: HUMAN OTC DRUG LABEL
Date: 20181117

ACTIVE INGREDIENTS: ZINC OXIDE 20 g/100 g
INACTIVE INGREDIENTS: CANDELILLA WAX; YELLOW WAX; HELIANTHUS ANNUUS SEED WAX; COCONUT OIL; RASPBERRY SEED OIL; ARGAN OIL; SIMMONDSIA CHINENSIS SEED WAX; ORANGE PEEL WAX; CARNAUBA WAX; VANILLA; COCOA BUTTER; SHEA BUTTER; TOCOPHEROL; MICA; BROWN IRON OXIDE

evanhealy Sheer Tint Sunscreen SPF30